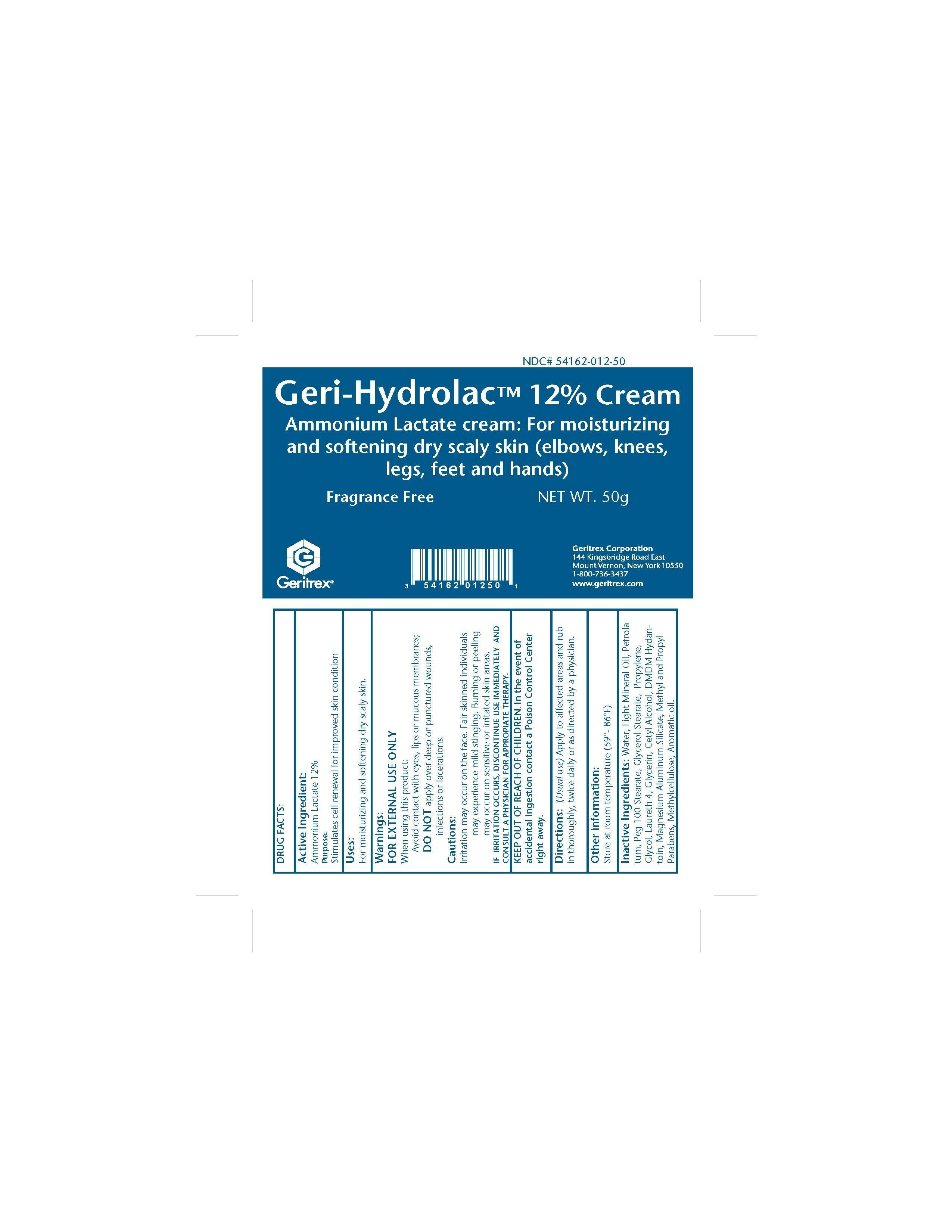 DRUG LABEL: Geri-Hydrolac
NDC: 54162-012 | Form: CREAM
Manufacturer: GERITREX CORP
Category: otc | Type: HUMAN OTC DRUG LABEL
Date: 20130625

ACTIVE INGREDIENTS: AMMONIUM LACTATE 12 g/100 g
INACTIVE INGREDIENTS: WATER; MINERAL OIL; PETROLATUM; PEG-100 STEARATE; PROPYLENE GLYCOL; LAURETH-4; GLYCERIN; CETYL ALCOHOL; DMDM HYDANTOIN; MAGNESIUM ALUMINUM SILICATE; METHYLPARABEN; PROPYLPARABEN; GUAR GUM

Geri-Hydrolac 12 Cream

Drug Facts

Active Ingredient: Ammonium lactate 12%

Purpose: Stimulates cell renewal for improved skin condition

Uses

For mosturizing and softening dry scaly skin

Directions

Apply to affected areas and rub in thoroughly, twice daily or as directed by a physician

WARNINGS

FOR EXTERNAL USE ONLY

When using this product

Avoid contact with eyes, lips or mucous membranes

Do not apply over deep or punctured wounds,

infections or lacerations.

Cautions: Irritation may occur on the face. Fair skinned individuals

may experience mild stinging. Burning or peeling may occur on sensitive or irritated skin areas.

If irritation occurs, Discontinue use immediately and consult a physcian for appropiate therapy.

Inactive Ingredient

Water, Light mineral oil, Petrolatum, Peg 100 stearate, Propylene Glycol,
Oleth 5, Glycerin, cetyl Alcohol, DMDM Hydantoin, Magnesium Aluminum silicate, Methyl and propyl paraben,
Guarcel

Keep out of reach of children. In the event of accidental ingestion contact a posion control center right away.

STORAGE AND HANDLING

Store at room temperature (59'-86'F)

DOSAGE AND ADMINISTRATION

Twice daily or as directed by a physician